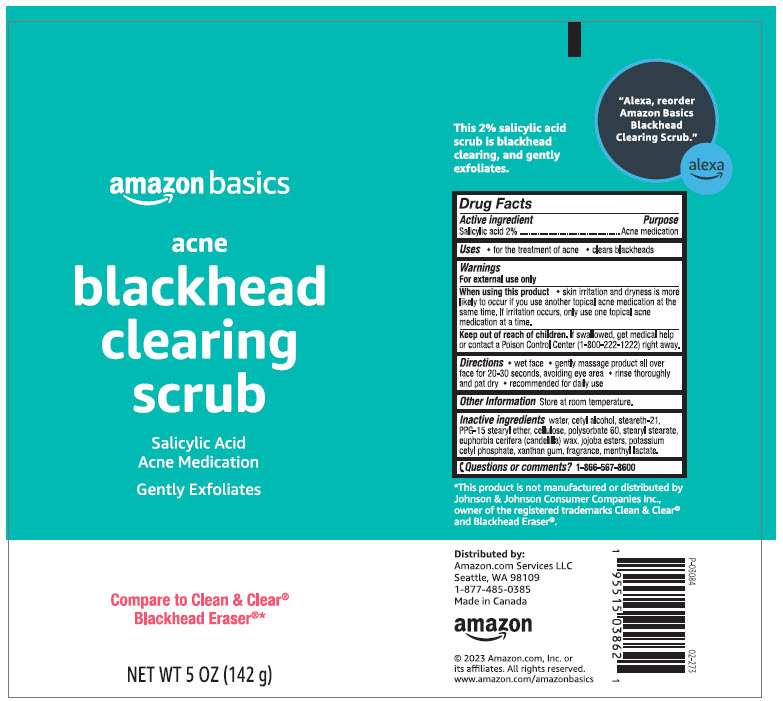 DRUG LABEL: amazon basics acne blackhead clearing scrub
NDC: 72288-862 | Form: LOTION
Manufacturer: AMAZON.COM SERVICES LLC
Category: otc | Type: HUMAN OTC DRUG LABEL
Date: 20241115

ACTIVE INGREDIENTS: Salicylic Acid 20 mg/1 g
INACTIVE INGREDIENTS: Water; Cetyl Alcohol; Steareth-21; POLYPROPYLENE GLYCOL 15 STEARYL ETHER; POWDERED CELLULOSE; Polysorbate 60; Stearyl Stearate; CANDELILLA WAX; Hydrolyzed Jojoba Esters (Acid Form); Potassium Cetyl Phosphate; Xanthan Gum; MENTHYL LACTATE, (-)-

amazon basics acne blackhead clearing scrub
Acne Treatment

Drug Facts

Active ingredient

Salicylic acid 2%

Purpose

Acne medication

Use

- for the treatment of acne
- clears blackheads

Warnings

For external use only

When using this product

- skin irritation and dryness is more likely to occur if you use another topical acne medication at the same time. If irritation occurs, only use one topical acne medication at a time.

Keep out of reach of children. If swallowed, get medical help or contact a Poison Control Center (1-800-222-1222) right away.

Directions

- wet face
- gently massage product all over face for 20-30 seconds, avoiding eye area
- rinse thoroughly and pat dry
- recommended for daily use

Other information

store at room temperature.

Inactive ingredients

water, cetyl alcohol, steareth-21, PPG-15 stearyl ether, cellulose, polysorbate 60, stearyl stearate, euphorbia cerifera (candelilla) wax, jojoba esters, potassium cetyl phosphate, xanthan gum, fragrance, menthyl lactate.

Questions or comments?

1-866-567-8600

Distributed by:
Amazon.com Services LLC
Seattle, WA 98109

PRINCIPAL DISPLAY PANEL - 142 g Tube Label

amazon basics

acne
blackhead
clearing
scrub

Salicylic Acid
Acne Medication

Gently Exfoliates

Compare to Clean & Clear®
Blackhead Eraser®*

NET WT 5 OZ (142 g)